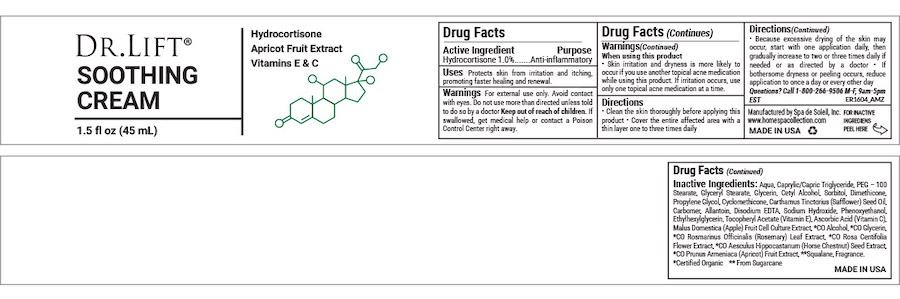 DRUG LABEL: Dr Lift Soothing Cream
NDC: 68062-2264 | Form: LOTION
Manufacturer: Spa de Soleil
Category: otc | Type: HUMAN OTC DRUG LABEL
Date: 20260121

ACTIVE INGREDIENTS: HYDROCORTISONE 0.45 mg/45 mL
INACTIVE INGREDIENTS: CYCLOMETHICONE 5; MEDIUM-CHAIN TRIGLYCERIDES; DIMETHICONE; WATER; CETYL ALCOHOL; PROPYLENE GLYCOL

Dr Lift Soothing Cream

Active Ingredient

Hydrocortisone 1%

Purpose

Anti-Inflammatory

Warnings

- For external use only.
- Avoid contact with the eyes
- If condition worsens or symptoms persist for more than seven days or clear up and occur again within a few days, stope use of this product and do not begin use of any hydrocortisone product until you have consulted a physician.
- Do not use for the treatment of diaper rash. Consult a physician.
- Keep out of reach of children.

Directions

• Clean the skin thoroughly before applying this product • Cover the entire affected area with a thin layer one to three times daily

Directions(Continued)

• Because excessive drying of the skin may occur, start with one application daily, then gradually increase to two or three times daily if needed or as directed by a doctor • If bothersome dryness or peeling occurs, reduce application to once a day or every other day

Uses:

Protects skin from irritation and itching, promoting faster healing and renewal.

Inactive Ingredients:

Water, Caprylic/Capric Triglyceride, Glyceryl Stearate SE, Glycerin, Dimethicone, Propylene Glycol, Cetyl Alcohol, Sorbitol, Carthamus Tinctorius (Safflower) Seed Oil, **Squalane, Carbomer, Lactic Acid, Peg-4, Morus Alba Root Extract, Glycyrrhiza Glabra (Licorice) Root Extract, Kojic Acid, Butylene Glycol, Arctostaphylos Uva-Ursi Leaf Extract, Sodium Hydroxide, Ruscus Aculeatus Root Extract, Ginkgo Biloba Leaf Extract, Diospyros Kaki Fruit Extract, Betula Alba Bark Extract, DMAE, Thioctic Acid, Ubiquinone, *CO Glycerin, Citric Acid, Malic Acid, Gluconic Acid, Ascorbic Acid (Vitamin C), Malus Domestica Fruit Cell Culture Extract, Glycolic Acid, Salicylic Acid, Tartaric Acid, *CO Humulus Lupulus (Hops) Extract, *CO Lavandula Angustifolia (Lavender) Flower/Leaf/Stem Extract, *CO Calendula Officinalis Flower Extract, *CO Chamomilla Recutita (Matricaria) Flower Extract, *CO Citrus Limon (Lemon) Peel Extract, *CO Cucumis Sativus (Cucumber) Seed Extract, *CO Camellia Sinensis Leaf Extract, *CO Pyrus Malus (Apple) Fruit Extract, *CO Spirulina Platensis Extract, Xanthan Gum, Lecithin, Tocopheryl Acetate (Vitamin E), Retinyl Palmitate (Vitamin A), Benzyl Alcohol, Dehydroacetic Acid

Warning

Keep out of reach of children.